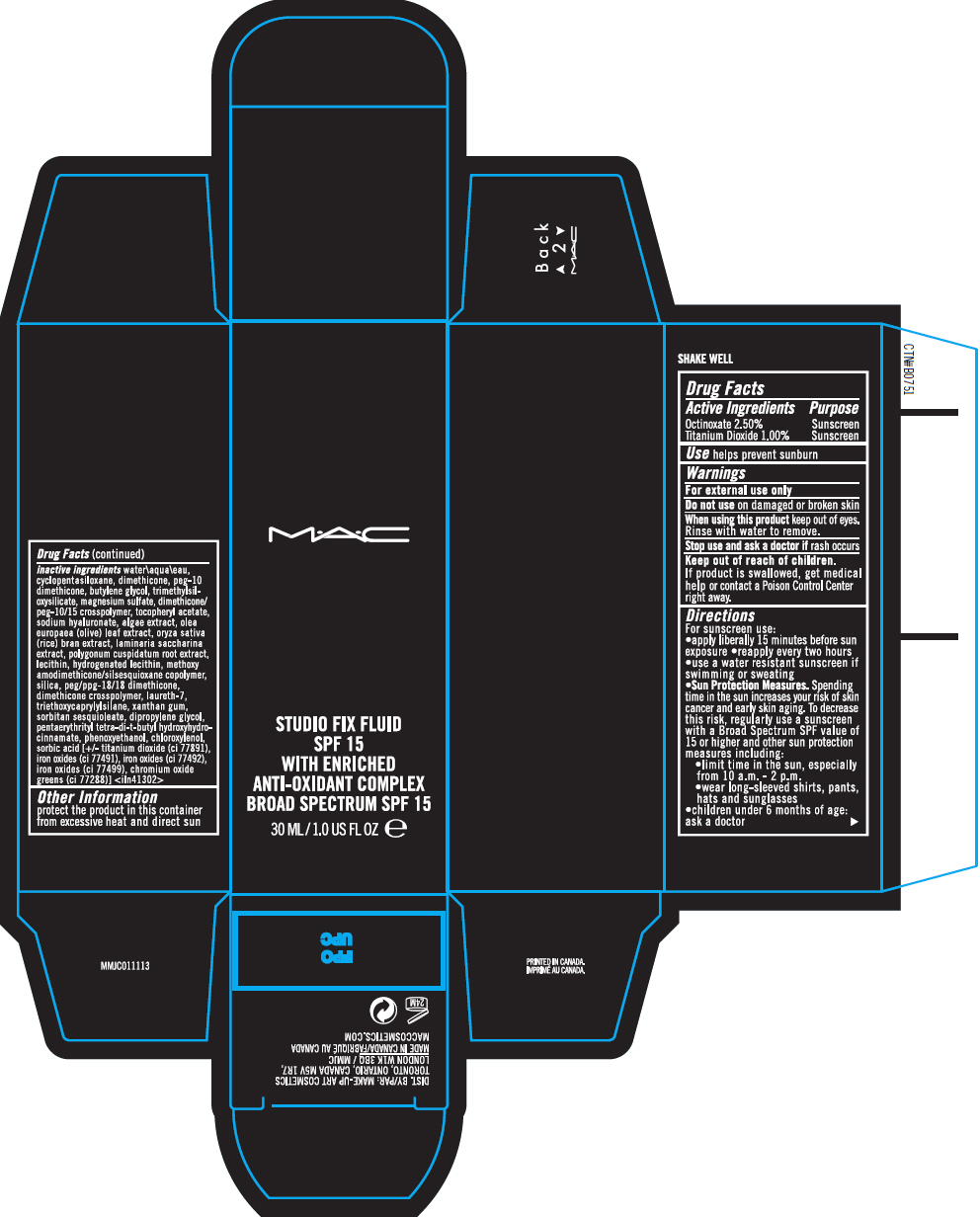 DRUG LABEL: STUDIO FIX FLUID BROAD SPECTRUM SPF 15 WITH ENRICHED ANTI-OXIDANT COMPLEX
NDC: 40046-0073 | Form: LOTION
Manufacturer: MAKEUP ART COSMETICS
Category: otc | Type: HUMAN OTC DRUG LABEL
Date: 20141202

ACTIVE INGREDIENTS: OCTINOXATE 0.02775 g/100 mL; TITANIUM DIOXIDE 0.0111 g/100 mL
INACTIVE INGREDIENTS: water; cyclomethicone 5; dimethicone; butylene glycol; magnesium sulfate; .alpha.-tocopherol acetate; hyaluronate sodium; olea europaea leaf; rice bran; saccharina latissima; polygonum cuspidatum root; silicon dioxide; peg/ppg-18/18 dimethicone; laureth-7; triethoxycaprylylsilane; xanthan gum; sorbitan sesquioleate; dipropylene glycol; pentaerythritol tetrakis(3-(3,5-di-tert-butyl-4-hydroxyphenyl)propionate); phenoxyethanol; chloroxylenol; sorbic acid; ferric oxide red; ferric oxide yellow; ferrosoferric oxide; chromic oxide

STUDIO FIX FLUID BROAD SPECTRUM SPF 15 WITH ENRICHED ANTI-OXIDANT COMPLEX

Drug Facts

ACTIVE INGREDIENT

Active Ingredients | Purpose
Octinoxate 2.50% | Sunscreen
Titanium Dioxide 1.00% | Sunscreen

Use

helps prevent sunburn

Warnings

For external use only

Do not use on damaged or broken skin

When using this product keep out of eyes. Rinse with water to remove.

Stop use and ask a doctor if rash occurs

Keep out of reach of children. If product is swallowed, get medical help or contact a Poison Control Center right away.

Directions

For sunscreen use:

- apply liberally 15 minutes before sun exposure
- reapply every two hours
- use a water resistant sunscreen if swimming or sweating
- Sun Protection Measures. Spending time in the sun increases your risk of skin cancer and early skin aging. To decrease this risk, regularly use a sunscreen with a Broad Spectrum SPF value of 15 or higher and other sun protection measures including:
  - limit time in the sun, especially from 10 a.m. - 2 p.m.
  - wear long-sleeved shirts, pants, hats and sunglasses
- children under 6 months of age: ask a doctor

inactive ingredients

water/aqua/eau, cyclopentasiloxane, dimethicone, peg-10 dimethicone, butylene glycol, trimethylsiloxysilicate, magnesium sulfate, dimethicone/peg-10/15 crosspolymer, tocopheryl acetate, sodium hyaluronate, algae extract, olea europaea (olive) leaf extract, oryza sativa (rice) bran extract, laminaria saccharina extract, polygonum cuspidatum root extract, lecithin, hydrogenated lecithin, methoxy amodimethicone/silsesquioxane copolymer, silica, peg/ppg-18/18 dimethicone, dimethicone crosspolymer, laureth-7, triethoxycaprylylsilane, xanthan gum, sorbitan sesquioleate, dipropylene glycol, pentaerythrityl tetra-di-t-butyl hydroxyhydrocinnamate, phenoxyethanol, chloroxylenol, sorbic acid [+/- titanium dioxide (ci 77891), iron oxides (ci 77491), iron oxides (ci 77492), iron oxides (ci 77499), chromium oxide greens (ci 77288)] <iln41302>

Other information

protect the product in this container from excessive heat and direct sun

DIST. BY: MAKE-UP ART COSMETICS
TORONTO, ONTARIO, CANADA M5V 1R7,
LONDON W1K 3BQ / MMJC

PRINCIPAL DISPLAY PANEL - 30 mL Tube Carton

M•A•C

STUDIO FIX FLUID
SPF 15
WITH ENRICHED
ANTI-OXIDANT COMPLEX
BROAD SPECTRUM SPF 15

30 ML/1.0 US FL OZ e